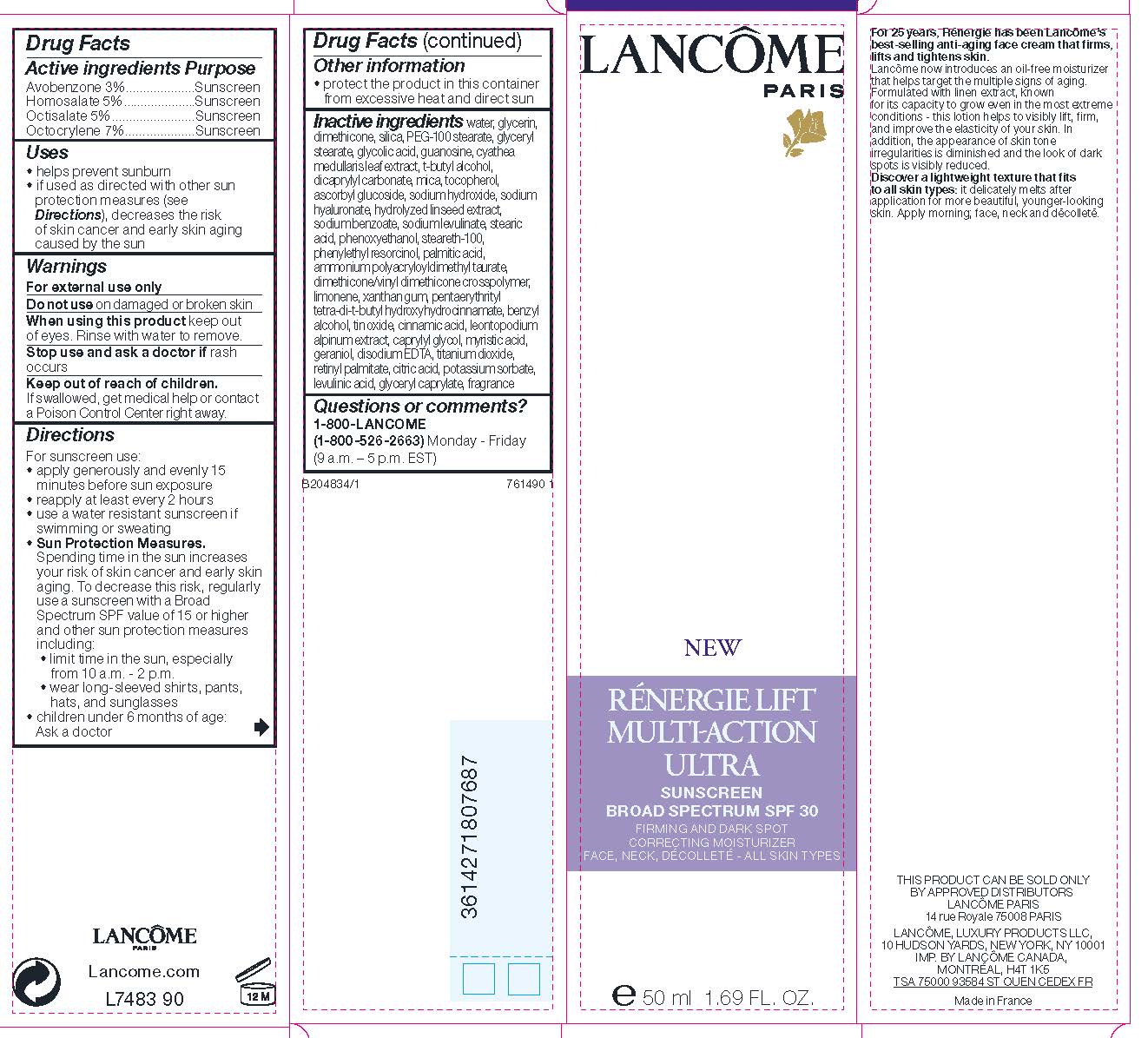 DRUG LABEL: Lancome Paris Renergie Lift MultiAction Ultra Firming and Dark Spot Correcting Moisturizer Broad Spectrum SPF 30 Sunscreen
NDC: 49967-768 | Form: LOTION
Manufacturer: L'Oreal USA Products Inc
Category: otc | Type: HUMAN OTC DRUG LABEL
Date: 20231230

ACTIVE INGREDIENTS: Avobenzone 30 mg/1 mL; HOMOSALATE 50 mg/1 mL; Octisalate 50 mg/1 mL; Octocrylene 70 mg/1 mL
INACTIVE INGREDIENTS: WATER; GLYCERIN; DIMETHICONE; SILICON DIOXIDE; PEG-100 STEARATE; GLYCERYL MONOSTEARATE; GLYCOLIC ACID; GUANOSINE; CYATHEA MEDULLARIS LEAF; TERT-BUTYL ALCOHOL; DICAPRYLYL CARBONATE; MICA; TOCOPHEROL; ASCORBYL GLUCOSIDE; SODIUM HYDROXIDE; HYALURONATE SODIUM; SODIUM BENZOATE; SODIUM LEVULINATE; STEARIC ACID; PHENOXYETHANOL; STEARETH-100; PHENYLETHYL RESORCINOL; PALMITIC ACID; DIMETHICONE/VINYL DIMETHICONE CROSSPOLYMER (HARD PARTICLE); LIMONENE, (+)-; XANTHAN GUM; PENTAERYTHRITOL TETRAKIS(3-(3,5-DI-TERT-BUTYL-4-HYDROXYPHENYL)PROPIONATE); BENZYL ALCOHOL; STANNIC OXIDE; CINNAMIC ACID; LEONTOPODIUM NIVALE SUBSP. ALPINUM ROOT; CAPRYLYL GLYCOL; MYRISTIC ACID; GERANIOL; EDETATE DISODIUM; TITANIUM DIOXIDE; VITAMIN A PALMITATE; CITRIC ACID MONOHYDRATE; POTASSIUM SORBATE; LEVULINIC ACID; GLYCERYL CAPRYLATE

Drug Facts

Active ingredients

Avobenzone 3%

Homosalate 5%

Octisalate 5%

Octocrylene 7%

Purpose

Sunscreen

Uses

- helps prevent sunburn
- if used as directed with other sun protection measures (see Directions), decreases the risk of skin cancer and early skin aging caused by the sun

Warnings

For external use only

Do not use

on damaged or broken skin

When using this product

keep out of eyes. Rinse with water to remove.

Stop use and ask a doctor if

rash occurs

Keep out of reach of children.

If swallowed, get medical help or contact a Poison Control Center right away.

Directions

For sunscreen use:

- apply generously and evenly 15 minutes before sun exposure
- reapply at least every 2 hours
- use a water resistant sunscreen if swimming or sweating
- Sun Protection Measures. Spending time in the sun increases your risk of skin cancer and early skin aging. To decrease this risk regularly use a sunscreen with a Broad Spectrum SPF value of 15 of higher and other sun protection measures including:
- limit time in the sun, especially from 10 a.m. - 2 p.m.
- wear long-sleeved shirts, pants, hats and sunglasses
- children under 6 months of age: Ask a doctor

Other information

- protect the product in this container from excessive heat and direct sun

Inactive ingredients

water, glycerin, dimethicone, silica, PEG-100 stearate, glyceryl stearate, glycolic acid, guanosine, cyathea medullaris leaf extract, t-butyl alcohol, dicaprylyl carbonate, mica, tocopherol, ascorbyl glycoside, sodium hydroxide, sodium hyaluronate, hydrolyzed linseed extract, sodium benzoate, sodium levulinate, stearic acid, phenoxyethanol, steareth-100, phenylethyl resorcinol, palmitic acid, ammonium polyacryloyldimethyl taurate, dimethicone/vinyl dimethicone crosspolymer, limonene, xanthan gum, pentaerythrityl tetra-di-t-butyl hydroxyhydrocinnamate, benzyl alcohol, tin oxide, cinnamic acid, leontopodium alpinum extract, caprylyl glycol, myristic acid, geraniol, disodium EDTA, titanium dioxide, retinyl palmitate, citric acid, potassium sorbate, levulinic acid, glyceryl pacrylate, fragrance

Questions or comments?

1-800-LANCOME (1-800-526-2663) Monday - Friday (9 a.m. - 5 p.m. EST)